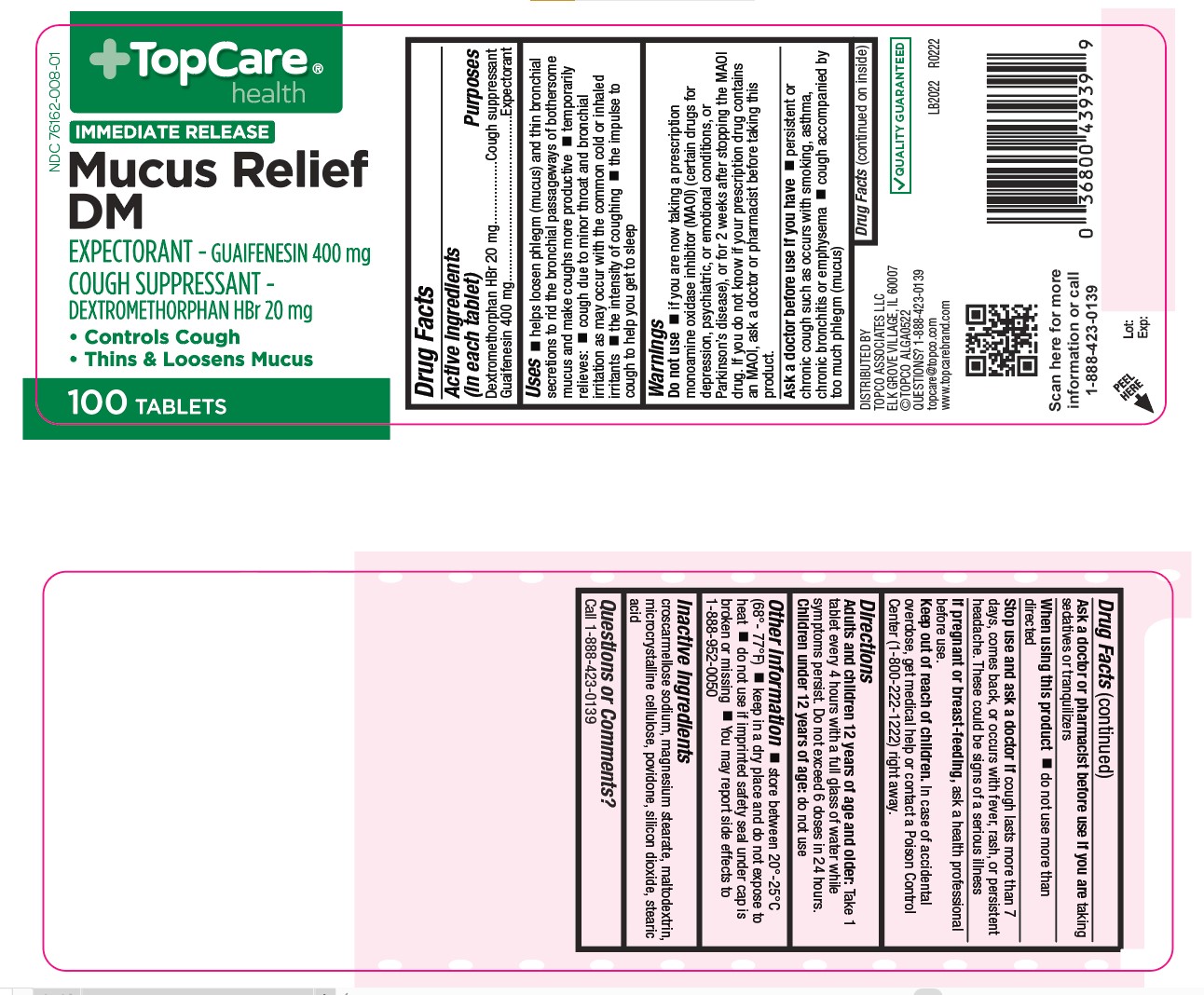 DRUG LABEL: Mucus Relief DM
NDC: 76162-008 | Form: TABLET
Manufacturer: TopCo Associates, LLC
Category: otc | Type: HUMAN OTC DRUG LABEL
Date: 20220607

ACTIVE INGREDIENTS: DEXTROMETHORPHAN HYDROBROMIDE 20 mg/1 1; GUAIFENESIN 400 mg/1 1
INACTIVE INGREDIENTS: CROSCARMELLOSE SODIUM; MAGNESIUM STEARATE; MALTODEXTRIN; MICROCRYSTALLINE CELLULOSE; POVIDONE; SILICON DIOXIDE; STEARIC ACID

432 - Mucus Relief DM

Active ingredient(s)

Dextromethorphan HBr 20 mg
Guaifenesin 400 mg

Purpose

Cough suppressant

Expectorant

Use(s)

- helps loosen phlegm (mucus) and thin bronchial secretions to rid the bronchial passageways of bothersome
  mucus and make coughs more productive
- temporarily relieves:
- cough due to minor throat and bronchial
  irritation as may occur with the common cold or inhaled irritants
- the intensity of coughing
- the impulse to cough to help you get to sleep

Warnings

Do not use

- if you are now taking a prescription
  monoamine oxidase inhibitor (MAOI) (certain drugs for
  depression, psychiatric, or emotional conditions, or
  Parkinson’s disease), or for 2 weeks after stopping the MAOI
  drug. If you do not know if your prescription drug contains
  an MAOI, ask a doctor or pharmacist before taking this
  product.

Ask a doctor before use if

- persistent or chronic cough such as occurs with smoking, asthma, chronic bronchitis or emphysema
- cough accompanied by too much phlegm (mucus)

Ask a doctor or pharmacist before use if

you are taking sedatives or tranquilizers

When using this product

- do not use more than directed

Stop use and ask a doctor if

cough lasts more than 7 days, comes back, or occurs with fever, rash, or persistent
headache. These could be signs of a serious illness

Pregnancy/Breastfeeding

ask a health professional before use.

Keep out of reach of children

In case of accidental overdose, get medical help or contact a Poison Control
Center (1-800-222-1222) right away.

Directions

Adults and children 12 years of age and older: Take 1 tablet every 4 hours with a

full glass of water while symptoms persist. Do not exceed 6 doses in 24 hours.

Children under 12 years of age: do not use

Other information

- store between 20°-25°C (68°- 77°F)
- keep in a dry place and do not expose to heat
- do not use if imprinted safety seal under cap is broken or missing
- You may report side effects to 1-888-952-0050

Inactive ingredients

croscarmellose sodium, magnesium stearate, maltodextrin, microcrystalline cellulose,
povidone, silicon dioxide, stearic acid

Questions

Questions or Comments?
Call 1-888-423-0139

Principal Display Panel

Mucus Relief DM